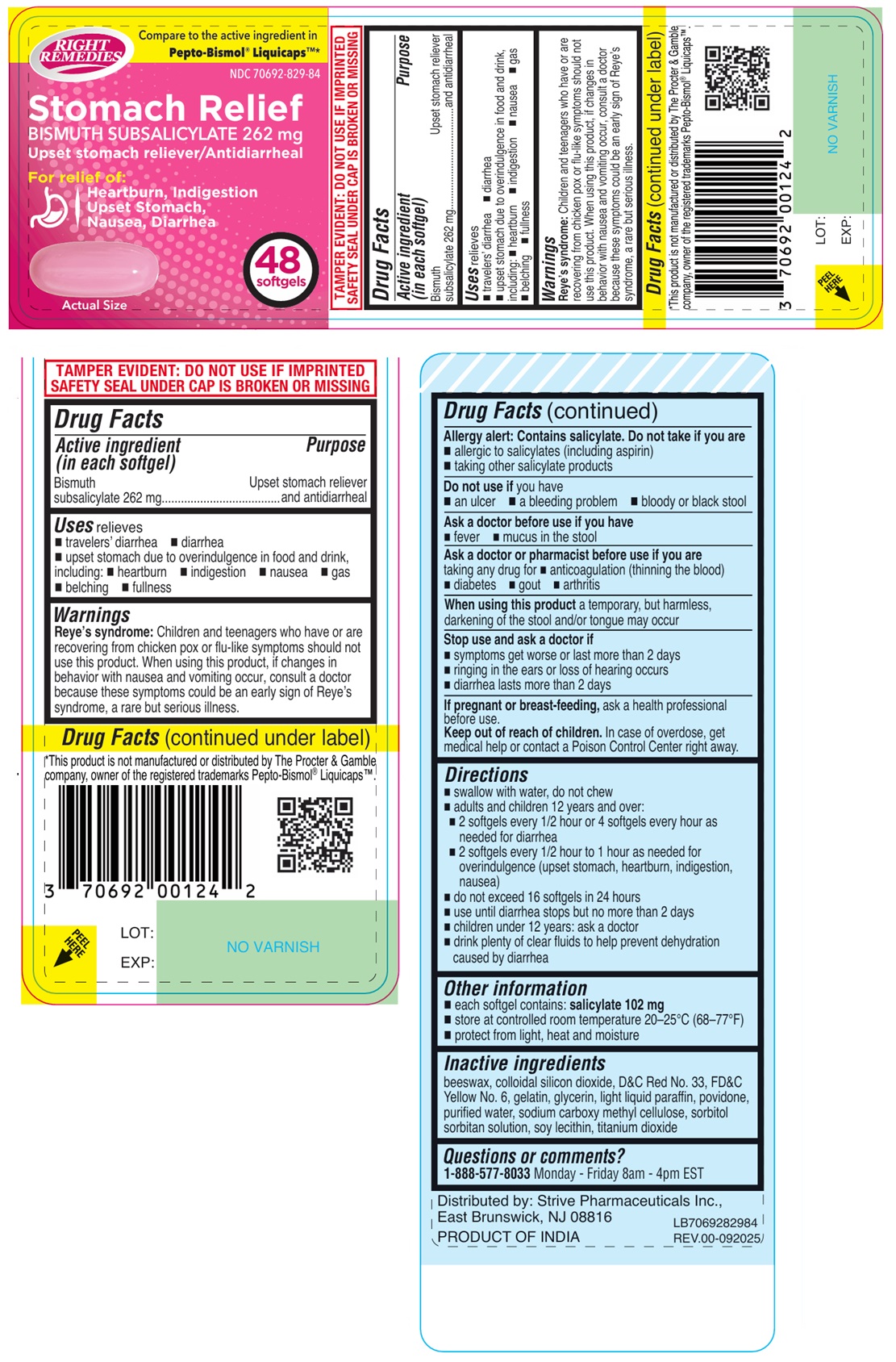 DRUG LABEL: RIGHT REMEDIES Stomach Relief BISMUTH SUBSALICYLATE 262 mg softgel
NDC: 70692-829 | Form: CAPSULE, LIQUID FILLED
Manufacturer: Strive Pharmaceuticals Inc.
Category: otc | Type: HUMAN OTC DRUG LABEL
Date: 20250922

ACTIVE INGREDIENTS: BISMUTH SUBSALICYLATE 262 mg/1 1
INACTIVE INGREDIENTS: YELLOW WAX; SILICON DIOXIDE; D&C RED NO. 33; FD&C YELLOW NO. 6; GELATIN, UNSPECIFIED; GLYCERIN; LIGHT MINERAL OIL; POVIDONE, UNSPECIFIED; WATER; CARBOXYMETHYLCELLULOSE SODIUM, UNSPECIFIED; SORBITOL; SORBITAN; SOYBEAN LECITHIN; TITANIUM DIOXIDE

RIGHT REMEDIES Stomach Relief BISMUTH SUBSALICYLATE 262 mg softgels

Active ingredient (in each softgel)

Bismuth subsalicylate 262 mg

Purpose

Upset stomach reliever and antidiarrheal

Uses

relieves
• travelers’ diarrhea • diarrhea
• upset stomach due to overindulgence in food and drink, including: • heartburn • indigestion • nausea • gas • belching • fullness

Warnings

Reye’s syndrome: Children and teenagers who have or are recovering from chicken pox or flu-like symptoms should not use this product. When using this product, if changes in behavior with nausea and vomiting occur, consult a doctor because these symptoms could be an early sign of Reye’s syndrome, a rare but serious illness.

Allergy alert: Contains salicylate. Do not take if you are
• allergic to salicylates (including aspirin)
• taking other salicylate products

Do not use if you have
• an ulcer • a bleeding problem • bloody or black stool

Ask a doctor before use if you have
• fever • mucus in the stool

Ask a doctor or pharmacist before use if you are
taking any drug for • anticoagulation (thinning the blood) • diabetes • gout • arthritis

When using this product a temporary, but harmless, darkening of the stool and/or tongue may occur

Stop use and ask a doctor if
• symptoms get worse or last more than 2 days
• ringing in the ears or loss of hearing occurs
• diarrhea lasts more than 2 days

If pregnant or breast-feeding, ask a health professional before use.

Keep out of reach of children. In case of overdose, get medical help or contact a Poison Control Center right away

Directions

• swallow with water, do not chew
• adults and children 12 years and over:
• 2 softgels every 1/2 hour or 4 softgels every hour as needed for diarrhea
• 2 softgels every 1/2 hour to 1 hour as needed for overindulgence (upset stomach, heartburn, indigestion, nausea)
• do not exceed 16 softgels in 24 hours
• use until diarrhea stops but no more than 2 days
• children under 12 years: ask a doctor
• drink plenty of clear fluids to help prevent dehydration caused by diarrhea

Other information

• each softgel contains: salicylate 102 mg
• store at controlled room temperature 20–25°C (68–77°F)
• protect from light, heat and moisture

Inactive ingredients

beeswax, colloidal silicon dioxide, D&C Red No. 33, FD&C Yellow No. 6, gelatin, glycerin, light liquid paraffin, povidone, purified water, sodium carboxy methyl cellulose, sorbitol sorbitan solution, soy lecithin, titanium dioxide

Questions or comments?

1-888-577-8033 Monday - Friday 8am - 4pm EST

Compare to the active ingredient in Pepto-Bismol® Liquicaps™*

Stomach Relief

For relief of:
Heartburn, Indigestion
Upset Stomach,
Nausea, Diarrhea

TAMPER EVIDENT: DO NOT USE IF IMPRINTED SAFETY SEAL UNDER CAP IS BROKEN OR MISSING

*This product is not manufactured or distributed by The Procter & Gamble company, owner of the registered trademarks Pepto-Bismol® Liquicaps™.

Distributed by: Strive Pharmaceuticals Inc.,
East Brunswick, NJ 08816

PRODUCT OF INDIA